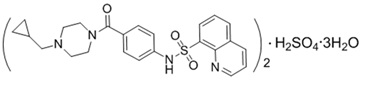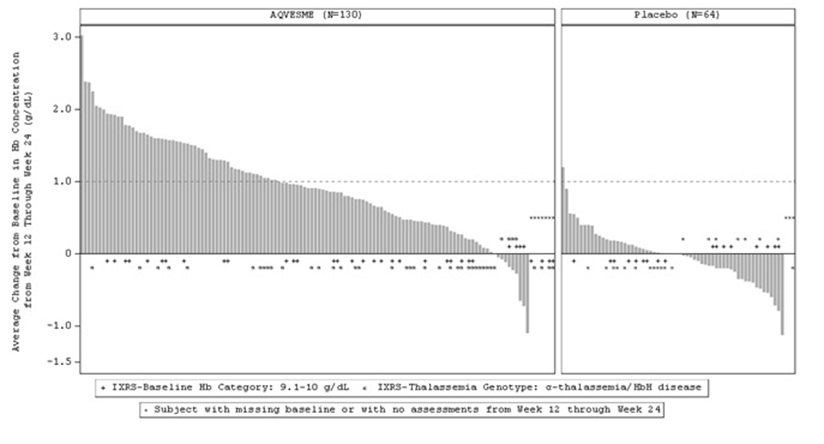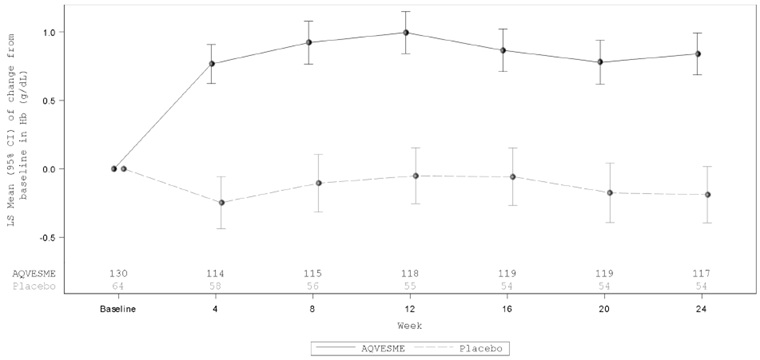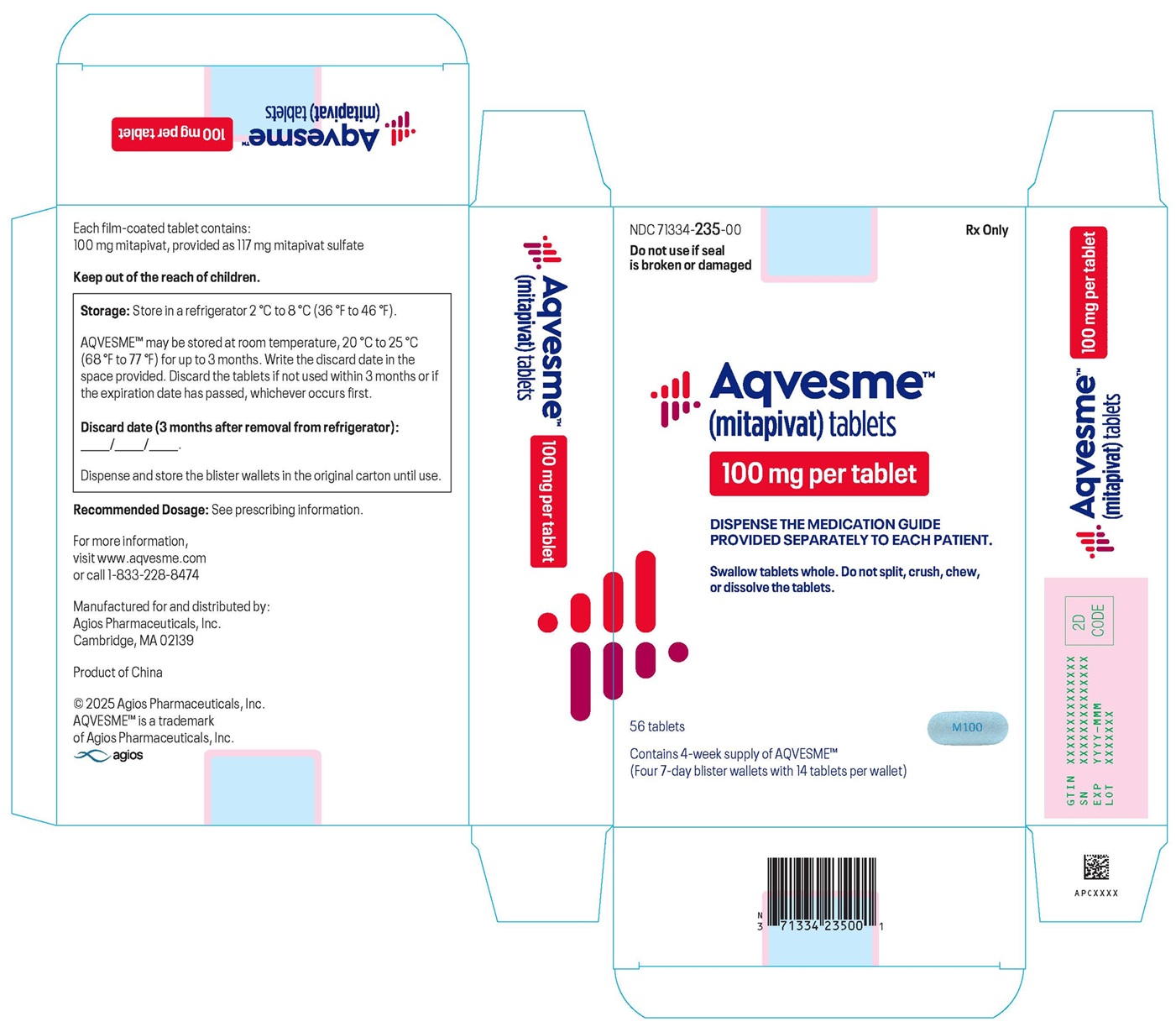 DRUG LABEL: AQVESME
NDC: 71334-235 | Form: TABLET, FILM COATED
Manufacturer: Agios Pharmaceuticals, Inc.
Category: prescription | Type: HUMAN PRESCRIPTION DRUG LABEL
Date: 20251229

ACTIVE INGREDIENTS: MITAPIVAT 100 mg/1 1
INACTIVE INGREDIENTS: CROSCARMELLOSE SODIUM; MANNITOL; MICROCRYSTALLINE CELLULOSE; SODIUM STEARYL FUMARATE; FD&C BLUE NO. 2; HYPROMELLOSE, UNSPECIFIED; LACTOSE MONOHYDRATE; TITANIUM DIOXIDE; TRIACETIN

HIGHLIGHTS OF PRESCRIBING INFORMATION

These highlights do not include all the information needed to use AQVESME safely and effectively. See full prescribing information for AQVESME.
AQVESME™ (mitapivat) tablets for oral use
Initial U.S. Approval: 2022

WARNING: HEPATOCELLULAR INJURY

See full prescribing information for complete boxed warning.

AQVESME can cause serious hepatocellular injury. Measure liver laboratory tests (ALT, AST, alkaline phosphatase, and total bilirubin with fractionation) at baseline and every 4 weeks for 24 weeks and then as clinically indicated. Avoid use of AQVESME in patients with cirrhosis. Discontinue AQVESME if hepatocellular injury is suspected. (5.1)

AQVESME is available only through a restricted program called the AQVESME REMS. (5.2)

1 INDICATIONS AND USAGE

AQVESME is a pyruvate kinase activator indicated for the treatment of anemia in adults with alpha- or beta-thalassemia. (1.1)

2 DOSAGE AND ADMINISTRATION

- The tablet should be swallowed whole. Do not split, crush, chew, or dissolve the tablets. (2.1)
- Recommended dose is 100 mg orally twice daily with or without food. (2.2)

3 DOSAGE FORMS AND STRENGTHS

Tablets: 100 mg. (3)

4 CONTRAINDICATIONS

None. (4)

6 ADVERSE REACTIONS

The most common adverse reactions were headache and insomnia. (6.1)

To report SUSPECTED ADVERSE REACTIONS, contact Agios Pharmaceuticals, Inc. at 1-833-228-8474 or FDA at 1-800-FDA-1088 or www.fda.gov/medwatch.

7 DRUG INTERACTIONS

- Strong CYP3A Inhibitors and Inducers: Avoid concomitant use. (7.1)
- Moderate CYP3A Inhibitors: Avoid concomitant use. (7.1)
- Moderate CYP3A Inducers: Consider alternatives that are not moderate inducers. If there are no alternatives, see Full Prescribing Information for recommended dosage for drug interactions with moderate CYP3A inducers. (2.4, 7.1)
- Sensitive CYP3A substrates including hormonal contraceptives: Avoid concomitant use with substrates that have narrow therapeutic index. (7.2)
- CYP2B6, CYP2C and UGT1A1 Substrates: Monitor patients for efficacy of the substrates with narrow therapeutic index. (7.2)
- P-gp Substrates: Monitor patients for adverse reactions of the substrates with narrow therapeutic index. (7.2)

8 USE IN SPECIFIC POPULATIONS

Hepatic Impairment: Avoid use of AQVESME in patients with cirrhosis (Child-Pugh Class A, B or C). (8.6)

FULL PRESCRIBING INFORMATION

WARNING: HEPATOCELLULAR INJURY

AQVESME can cause serious hepatocellular injury. Measure liver laboratory tests (ALT, AST, alkaline phosphatase, and total bilirubin with fractionation) at baseline and every 4 weeks for 24 weeks and then as clinically indicated. Avoid use of AQVESME in patients with cirrhosis. Discontinue AQVESME if hepatic injury is suspected [see Warnings and Precautions (5.1)].

Because of the risk of hepatocellular injury, AQVESME is available only through a restricted program under a Risk Evaluation and Mitigation Strategy (REMS) called the AQVESME REMS [see Warnings and Precautions (5.2)].

1 INDICATIONS AND USAGE

AQVESME is indicated for the treatment of anemia in adults with alpha- or beta-thalassemia.

2 DOSAGE AND ADMINISTRATION

2.1 Important Dosage and Administration Information

- AQVESME is taken with or without food.
- Swallow tablets whole. Do not split, crush, chew, or dissolve the tablets.
- If a dose of AQVESME is missed by 4 hours or less, administer the dose as soon as possible. If a dose of AQVESME is missed by more than 4 hours, do not administer a replacement dose, and wait until the next scheduled dose. Subsequently, return to the normal dosing schedule.
- Monitor for hepatocellular injury during treatment with AQVESME [see Dosage and Administration (2.3)].

2.2 Recommended Dosage

The recommended dosage for adults with alpha- or beta-thalassemia is AQVESME 100 mg orally twice daily.

Treatment with AQVESME is intended to be long-term. Discontinue AQVESME if no benefit in hemolytic anemia has been observed, based on the totality of laboratory results and clinical status of the patient, unless there is another explanation for response failure (e.g., bleeding, surgery, other concomitant illnesses).

Interruption or Discontinuation

If a patient needs to interrupt or discontinue AQVESME for any reason, a dose taper is not necessary.

2.3 Monitoring for Safety

Prior to Initiating Treatment with AQVESME

- Check liver tests including ALT, AST, alkaline phosphatase, total bilirubin with fractionation, before first AQVESME dose.

During Treatment with AQVESME

- After the first dose, check liver tests including ALT, AST, alkaline phosphatase, total bilirubin with fractionation every 4 weeks for 24 weeks and as clinically indicated thereafter.

When Drug-Induced Liver Injury Is Suspected

- Interrupt AQVESME and complete a comprehensive evaluation to rule out other causes of liver injury.
- If AQVESME-related liver injury caused new or worsening jaundice or ALT ≥10×baseline, do NOT restart AQVESME.
- If AQVESME-related liver injury is not ruled out, but peak ALT is <10×baseline without elevation of bilirubin above baseline, and if AQVESME is resumed, reinitiate liver test monitoring every 4 weeks for 24 additional weeks.
- If AQVESME-related liver injury is ruled out, AQVESME may be restarted at provider discretion. Resume liver test monitoring schedule that existed prior to stopping AQVESME.

AQVESME Interruption Due to Non-Liver Causes

- If AQVESME was stopped for any reason for ≤8 weeks other than suspected AQVESME-related liver injury, resume the liver test monitoring schedule that existed prior to stopping AQVESME.
- If AQVESME was stopped for more than 8 weeks, restart liver test monitoring every 4 weeks for 24 additional weeks upon resumption of treatment with AQVESME.
- If treatment is stopped for any duration after 24 weeks of monitoring and treatment, resume monitoring as clinically indicated.

2.4 Recommended Dosage for Drug Interactions

Moderate CYP3A Inducers

Consider alternative therapies that are not moderate CYP3A inducers during treatment with AQVESME. If there are no alternative therapies, monitor Hb and do not exceed the maximum recommended dose of 100 mg orally twice daily [see Drug Interactions (7.1) and Clinical Pharmacology (12.3)].

3 DOSAGE FORMS AND STRENGTHS

- 100 mg tablets: oblong, blue, film-coated tablets with "M100" printed on both sides.

4 CONTRAINDICATIONS

None.

5 WARNINGS AND PRECAUTIONS

5.1 Hepatocellular Injury

AQVESME can cause hepatocellular injury. Avoid use of AQVESME in patients with cirrhosis. In patients with thalassemia treated with AQVESME, liver injury with and without jaundice has been observed within the first 6 months of exposure. Obtain liver tests (including ALT, AST, alkaline phosphatase, total bilirubin with fractionation) prior to the initiation of AQVESME, then every 4 weeks for the first 24 weeks, and as clinically indicated thereafter. Interrupt AQVESME if clinically significant increases in liver tests are observed or alanine aminotransferase is >5 times the upper limit of normal (ULN). Complete a comprehensive evaluation to rule out other causes of liver injury when drug-induced liver injury (DILI) is suspected. Discontinue AQVESME if hepatocellular injury due to AQVESME is suspected [see Dosage and Administration (2.3)].

Symptoms and signs of early liver injury may mimic those of thalassemia. Advise patients to report new or worsening symptoms of loss of appetite, nausea, right upper quadrant abdominal pain, vomiting, scleral icterus, jaundice, or dark urine while on AQVESME treatment.

During the double-blind period, 2 of 301 patients (0.66%) with thalassemia treated with AQVESME experienced adverse reactions suggestive of hepatocellular injury. Three additional patients experienced adverse reactions suggestive of hepatocellular injury during the open-label extension periods after switching from placebo to AQVESME. Of these 5 patients, two had serious liver injury and were hospitalized including 1 patient who developed jaundice (peak bilirubin 32 mg/dL). Another patient developed jaundice (peak bilirubin 4 mg/dL) without being hospitalized. These reactions were characterized by a time to onset within the first 6 months of treatment with peak elevations of alanine aminotransferase of >5×ULN with or without jaundice. All patients discontinued treatment with AQVESME, and these reactions improved upon treatment discontinuation.

AQVESME is available only through a restricted program under a REMS [see Warnings and Precautions (5.2)].

5.2 AQVESME REMS

AQVESME is available only through a restricted program under a REMS called the AQVESME REMS because of the risk of hepatocellular injury.

Notable requirements of the AQVESME REMS include the following:

- Prescribers must be certified by enrolling in the REMS and completing training.
- Prescribers must counsel patients receiving AQVESME about the risk of hepatocellular injury.
- Prescribers must monitor liver tests (including ALT, AST, alkaline phosphatase, total bilirubin with fractionation, and other tests as clinically indicated) to determine if the patient is appropriate to receive AQVESME treatment.
- Patients must enroll in the REMS and comply with the monitoring requirements.
- Pharmacies must be certified by enrolling in the REMS and must only dispense to patients who are authorized to receive AQVESME.

Further information is available at www.aqvesmerems.com or 1-800-625-9951.

6 ADVERSE REACTIONS

The following clinically significant adverse reaction is described elsewhere in labeling:

- Hepatocellular Injury [see Warnings and Precautions (5.1)].

6.1 Clinical Trials Experience

Because clinical trials are conducted under widely varying conditions, adverse reaction rates observed in the clinical trials of a drug cannot be directly compared to rates in the clinical trials of another drug and may not reflect the rates observed in practice.

Alpha- and Beta-Thalassemia

A total of 301 patients with thalassemia received AQVESME, administered at 100 mg orally twice daily, for up to 59.9 weeks in the ENERGIZE trial (N=129) and the ENERGIZE-T trial (N=172) [see Clinical Studies (14)].

ENERGIZE Trial

Patients with non-transfusion-dependent thalassemia received AQVESME (N=129) or placebo (N=63).

The most common adverse reactions (≥5% and at least 5% higher in the AQVESME arm) in patients with non-transfusion-dependent thalassemia were headache and insomnia.

ENERGIZE-T Trial

Patients with transfusion-dependent thalassemia received AQVESME (N=172) or placebo (N=85).

The most common adverse reactions (≥5% and at least 5% higher in the AQVESME arm) in patients with transfusion-dependent thalassemia were headache and insomnia.

Serious adverse reactions occurred in 1.3% of patients with thalassemia treated with AQVESME, including supraventricular arrhythmia and supraventricular tachycardia. Permanent discontinuations of AQVESME due to an adverse reaction occurred in 1.3% of patients and included elevated hepatic transaminases and insomnia.

Table 1 summarizes the adverse reactions in the ENERGIZE and the ENERGIZE-T trials, individually and combined.

Table 1: Adverse Reactionsa in Patients with Alpha- and Beta-Thalassemia Receiving AQVESME
 | ENERGIZE (Non-transfusion-dependent) |  | ENERGIZE-T (Transfusion-dependent) |  | Total
Adverse Reactions | AQVESME (N=129) n (%) | Placebo (N=63) n (%) | AQVESME (N=172) n (%) | Placebo (N=85) n (%) | AQVESME (N=301) n (%) | Placebo (N=148) n (%)
Headache | 29 (22.5) | 6 (9.5) | 46 (26.7) | 10 (11.8) | 75 (24.9) | 16 (10.8)
Insomniab | 35 (27.1) | 5 (7.9) | 38 (22.1) | 8 (9.4) | 73 (24.3) | 13 (8.8)
a Included adverse reactions that occurred in at least 5% of patients in the AQVESME arm and at least 5% higher than the placebo arm.
b Term includes initial insomnia, middle insomnia, and terminal insomnia.

Variations in Reproductive Hormones

Increases in serum testosterone (T) concentrations and decreases in serum estradiol (E2) concentrations were observed in men receiving AQVESME (Table 2). These changes in hormones were maintained during treatment with AQVESME. In 3 male patients who discontinued AQVESME and in whom reproductive hormone data were available following discontinuation of AQVESME, the hormone changes were reversible. In female patients, sex hormone analysis was limited due to physiologic variations in hormones during the menstrual cycle and the use of hormonal contraceptives.

Table 2: Abnormalities in Reproductive Hormones in Men with Thalassemia Receiving AQVESME
 | ENERGIZE (Non-transfusion-dependent) |  | ENERGIZE-T (Transfusion-dependent)
Parameter | AQVESME (46 males) | Placebo (25 males) | AQVESME (64 males) | Placebo (31 males)
Reproductive hormone analyses
Testosterone (T)
Serum T concentration (mean) Baseline Change from baseline | 613 ng/dL 228 ng/dL | 505 ng/dL -2.8 ng/dL | 625 ng/dL 108 ng/dL | 666 ng/dL 66 ng/dL
Serum T increaseda Baseline Change from baseline | 2.2% 18.6% | 4.3% 0% | 3.3% 13.5% | 10% 6.9%
Estradiol (E2)
Serum E2 concentration (mean) Baseline Change from baseline | 29.6 pg/mL -8.7 pg/mL | 27.3 pg/mL 0 pg/mL | 26.4 pg/mL -5.0 pg/mL | 28.9 pg/mL 1.6 pg/mL
Serum E2 decreasedb Baseline Change from baseline | 0% 2.5% | 9.5% 0% | 10.2% 8.5% | 6.9% 3.6%
a Percentage of subjects with serum T concentration above the upper limit of normal (greater than 1050 ng/dL) at baseline and percentage of subjects with serum T increases from baseline to above the upper limit of normal where baseline was within normal limits.
b Percentage of subjects with serum E2 concentration below the lower limit of normal at baseline and percentage of subjects with serum E2 decreases from baseline to below the lower limit of normal where baseline was within normal limits.
Note: Results from the ENERGIZE-T study do not include data from patients who received concomitant testosterone replacement therapies.

7 DRUG INTERACTIONS

7.1 Effect of Other Drugs on AQVESME

Strong CYP3A Inhibitors
Clinical Impact | - Co-administration of AQVESME with strong CYP3A inhibitors increased mitapivat plasma concentrations [see Clinical Pharmacology (12.3)]. - Increased mitapivat plasma concentrations may increase the risks of adverse reactions of AQVESME.
Prevention or Management | - Avoid co-administration of strong CYP3A inhibitors with AQVESME [see Dosage and Administration (2.4)].
Moderate CYP3A Inhibitors
Clinical Impact | - Co-administration of AQVESME with moderate CYP3A inhibitors will increase mitapivat plasma concentrations [see Clinical Pharmacology (12.3)].
Prevention or Management | - Avoid co-administration of moderate CYP3A inhibitors with AQVESME [see Dosage and Administration (2.4)].
Strong CYP3A Inducers
Clinical Impact | - Co-administration of AQVESME with strong CYP3A inducers decreased mitapivat plasma concentrations [see Clinical Pharmacology (12.3)]. - Decreased mitapivat plasma concentrations will reduce the efficacy of AQVESME.
Prevention or Management | - Avoid co-administration of strong CYP3A inducers with AQVESME [see Dosage and Administration (2.4)].
Moderate CYP3A Inducers
Clinical Impact | - Co-administration of AQVESME with moderate CYP3A inducers will decrease mitapivat plasma concentrations [see Clinical Pharmacology (12.3)].
Prevention or Management | - Consider alternative therapies that are not moderate CYP3A inducers during treatment with AQVESME. If there are no alternative therapies, monitor Hb and do not exceed the maximum recommended dose of 100 mg twice daily [see Dosage and Administration (2.4)].

7.2 Effect of AQVESME on Other Drugs

CYP3A Substrates
Clinical Impact | - AQVESME induces CYP3A. Co-administration of AQVESME will decrease systemic concentrations of drugs that are sensitive CYP3A substrates, including hormonal contraceptives (e.g., ethinyl estradiol) [see Clinical Pharmacology (12.3)].
Prevention or Management | - Avoid co-administration of AQVESME with sensitive CYP3A substrates that have narrow therapeutic index when co-administered with AQVESME. - Avoid concomitant use with hormonal contraceptives except for intrauterine systems containing levonorgestrel. If contraception is desired or needed, use an alternative contraceptive that is not affected by enzyme inducers. If concomitant use is unavoidable, use additional nonhormonal contraception during concomitant use and for 28 days after discontinuation of AQVESME.
CYP2B6 and CYP2C Substrates
Clinical Impact | - AQVESME induces CYP2B6, CYP2C8, CYP2C9, and CYP2C19 enzymes in vitro, and may decrease systemic concentrations of drugs that are sensitive substrates of these enzymes [see Clinical Pharmacology (12.3)].
Prevention or Management | - Monitor patients for loss of therapeutic effect of sensitive substrates of these enzymes with narrow therapeutic index when co-administered with AQVESME.
UGT1A1 Substrates
Clinical Impact | - AQVESME induces UGT1A1 in vitro and may decrease systemic concentrations of drugs that are UGT1A1 substrates [see Clinical Pharmacology (12.3)].
Prevention or Management | - Monitor patients for loss of therapeutic effect of UGT1A1 substrates with narrow therapeutic index when co-administered with AQVESME.
P-gp Substrates
Clinical Impact | - AQVESME inhibits the P-gp transporter in vitro and may increase systemic concentrations of drugs that are P-gp substrates [see Clinical Pharmacology (12.3)].
Prevention or Management | - Monitor patients for adverse reactions of P-gp substrates with narrow therapeutic index when co-administered with AQVESME.

8 USE IN SPECIFIC POPULATIONS

8.1 Pregnancy

Risk Summary

Available data from clinical trials of AQVESME are insufficient to evaluate for a drug-associated risk of major birth defects, miscarriage or other adverse maternal or fetal outcomes.

In animal reproduction studies, mitapivat orally administered twice daily to pregnant rats and rabbits during organogenesis was not teratogenic at exposures up to 9.9- and 2.4‑fold the human exposure associated with the MRHD, respectively. Mitapivat administered orally to pregnant rats twice daily during organogenesis through lactation did not result in adverse developmental effects at doses up to 9.9 times the MRHD (see Data).

The estimated background risk of major birth defects for the indicated population is unknown. All pregnancies have a background risk of birth defect, loss, or other adverse outcomes. In the U.S. general population, the estimated background risk of major birth defects and miscarriage in clinically recognized pregnancies is 2% to 4% and 15% to 20%, respectively.

Clinical Considerations

Disease-Associated Maternal Risk

Transfusion requirements in thalassemia patients are increased during pregnancy. Pregnant women with transfusion-dependent thalassemia are considered high risk, with their major complications being cardiac in origin, including cardiac dysrhythmia, right ventricular dysfunction, and cardiac failure, reported in 1.1% to 15.6%. Pregnant women with non-transfusion-dependent thalassemia need to be monitored and treated for risk of thrombosis, especially those who are splenectomized or infrequently transfused. Patients with non-transfusion-dependent thalassemia may develop a need for regular transfusions during pregnancy, and in such patients the risk of alloimmunization should be carefully evaluated. All pregnant women with thalassemia should be closely monitored for iron overload.

Data

Animal Data

In an embryo-fetal development study in rats, mitapivat was administered at doses of 5, 10, 25, and 100 mg/kg twice daily by oral gavage during the period of organogenesis (gestation days 6 to 17). There was a statistically significant 14% decrease in maternal net body weight gain at 100 mg/kg twice daily with associated decrease in food consumption. Enlarged or fused placenta and/or a distended amniotic sac, an increase in post-implantation loss (early and late resorptions), a decrease in the mean number of viable fetuses, lower mean fetal weights, and fetal external, visceral, and skeletal malformations were observed at 100 mg/kg twice daily, (48 times the MRHD, based on area under the plasma drug concentration-time curve [AUC]). No maternal or embryo-fetal toxicity was observed up to 25 mg/kg twice daily (9.9 times the MRHD, based on AUC).

In an embryo-fetal development study in rabbits, mitapivat was administered at doses of 12.5, 30, and 62.5 mg/kg twice daily by oral gavage during the period of organogenesis (gestation days 7 to 20). Lower fetal weight was observed at 62.5 mg/kg twice daily (2.4 times MRHD, based on AUC) and correlated with reduced maternal body weight gain. No effects on fetal morphology were observed.

In a pre- and post-natal development study in rats, mitapivat was administered at doses of 5, 10, 25, and 100 mg/kg twice daily by oral gavage during the period of organogenesis and continuing to weaning (gestation day 7 to lactation day 20). Dystocia was observed at ≥25 mg/kg twice daily (≥9.9 times MRHD, based on AUC). At 100 mg/kg twice daily (48 times MRHD, based on AUC) decreased maternal body weight gain, prolonged parturition, and dystocia occurred and resulted in maternal mortality, complete litter loss, decreased pup viability and decreased pup body weight. No adverse effects on pup growth and development, and reproductive performance were observed up to 50 mg/kg (9.9 times the MRHD, based on AUC).

8.2 Lactation

Risk Summary

There are no data on the presence of AQVESME or its metabolites in human or animal milk, the effects on the breastfed child, or the effects on milk production. The developmental and health benefits of breastfeeding should be considered along with the mother’s clinical need for AQVESME and any potential adverse effects on the breastfed child from AQVESME or from the underlying maternal condition.

8.4 Pediatric Use

Safety and effectiveness in pediatric patients have not been established.

8.5 Geriatric Use

Clinical studies of AQVESME did not include sufficient numbers of subjects aged 65 years and over to determine whether they respond differently from younger subjects.

8.6 Hepatic Impairment

Avoid use in patients with cirrhosis (Child-Pugh Class A, B, or C) due to an increased risk of severe outcomes if hepatocellular injury occurs [see Warnings and Precautions (5.1)]. In patients with cirrhosis Child-Pugh Class B and C, there is a potential increase in AQVESME exposure [see Clinical Pharmacology (12.3)].

11 DESCRIPTION

The active ingredient of AQVESME is mitapivat, a pyruvate kinase activator, present as mitapivat sulfate. The chemical name of mitapivat sulfate is 8-quinolinesulfonamide, N-[4-[[4- (cyclopropylmethyl)-1-piperazinyl]carbonyl]phenyl]-, sulfate, hydrate (2:1:3). The chemical structure of mitapivat sulfate is:

The molecular formula is (C24H26N4SO3)2 • H2SO4 • 3H2O, and the molecular weight is 1053.23 for mitapivat sulfate. Mitapivat sulfate is a white to off-white solid and is slightly soluble in water.

AQVESME is available as 100 mg tablets for oral administration. Each tablet contains 100 mg mitapivat free base, provided as 117.0 mg of the sulfate hydrate salt, and the following inactive ingredients: croscarmellose sodium, mannitol, microcrystalline cellulose, and sodium stearyl fumarate.

The 100 mg tablet film coating contains the inactive ingredients FD&C Blue No. 2, hypromellose, lactose monohydrate, titanium dioxide, triacetin, and macrogol/PEG. The tablets are imprinted with blue ink containing the inactive ingredients ammonium hydroxide, FD&C Blue No. 1, isopropyl alcohol, n-butyl alcohol, propylene glycol, shellac glaze, and titanium dioxide.

12 CLINICAL PHARMACOLOGY

12.1 Mechanism of Action

Mitapivat is a pyruvate kinase activator that acts by allosterically binding to the pyruvate kinase tetramer and increasing pyruvate kinase (PK) activity. Imbalances in globin chain production during erythropoiesis result in increased oxidative stress, which leads to ineffective erythropoiesis and hemolysis. In nonclinical models of beta-thalassemia, mitapivat improved energy homeostasis, RBC longevity, ineffective erythropoiesis, and hemolysis by increasing PK activity.

12.2 Pharmacodynamics

Mitapivat decreases 2,3 diphosphoglycerate (2,3-DPG) and increases ATP in healthy volunteers and in patients with thalassemia.

Cardiac Electrophysiology

At a dose 3 times the recommended dose, mitapivat did not prolong the QT interval to any clinically relevant extent.

12.3 Pharmacokinetics

The population pharmacokinetic model simulated Cmax, Ctrough, AUC0-12 and accumulation ratio of mitapivat at the recommended dosage is listed in Table 3.

Table 3: Steady State Mitapivat Exposure at the Recommended Dosagea
Mitapivat Dosage | Cmax (ng/mL) | Ctrough (ng/mL) | AUC 0-12 (ng*h/mL) | Accumulation Ratio
100 mg twice daily b | 1641.7 (12.9%) | 71 (18.5%) | 4835.6 (5.8%) | 0.83
a Pharmacokinetic parameters are presented as geometric mean (CV%). The interval of the last 12 hours was selected for steady state PK parameters calculation. Residual error was not included during simulation.
b The simulations were performed at steady state.

Absorption

Median tmax values at steady state were 0.5 to 1.0 hour post-dose at 100 mg twice daily.

The absolute bioavailability after a single dose was approximately 73%.

Effect of Food

Following administration of a single dose of AQVESME in healthy subjects, a high-fat meal (approximately 900 to 1,000 total calories, with 500 to 600 calories from fat, 250 calories from carbohydrate, and 150 calories from protein) did not change the exposure (AUCinf) of mitapivat, but reduced the rate of mitapivat absorption, with a 42% reduction in Cmax and a delay in tmax of 2.3 hours when compared to dosing under fasted conditions.

Distribution

Mitapivat is highly protein bound (97.7%) in plasma with low RBC distribution (RBC-to-plasma ratio of 0.37). The mean volume of distribution at steady state (Vss) was 42.5 L.

Elimination

Population pharmacokinetics derived median CL/F at steady state was 17.7 L/h at 100 mg twice daily.

Metabolism

In vitro studies showed that mitapivat is primarily metabolized by CYP3A4. Following a single oral dose of 120 mg of radiolabeled mitapivat to healthy subjects, unchanged mitapivat was the major circulating component.

Excretion

After a single oral administration of radiolabeled mitapivat to healthy subjects, the total recovery of administered radioactive dose was 89.2%, with 49.6% in the urine (2.6% unchanged) and 39.6% in the feces (<1% unchanged).

Specific Populations

No clinically meaningful effects on the pharmacokinetics of mitapivat were observed based on age, sex, race, or body weight.

Pediatric Population

The pharmacokinetics of mitapivat in children and adolescents (˂18 years old) have not been studied.

Hepatic Impairment

Mitapivat undergoes extensive hepatic metabolism. The pharmacokinetics of mitapivat were studied in adult subjects with moderate hepatic impairment (Child-Pugh Class B). After a single oral administration of 50 mg mitapivat, subjects with moderate hepatic impairment demonstrated 36% greater exposure (AUC∞) to mitapivat, compared to subjects with normal hepatic function. Geometric mean Cmax values were similar between the groups. There were no major changes to plasma protein binding or elimination half-life in subjects with moderate hepatic impairment relative to healthy controls. The pharmacokinetics of mitapivat in subjects with severe hepatic impairment (Child-Pugh Class C) have not been studied.

Renal Impairment

The effects of renal impairment on mitapivat pharmacokinetics were assessed with population pharmacokinetic analyses. Steady state AUC of mitapivat in patients with eGFR 60 to <90 mL/min/1.73 m^2 was not significantly different compared to patients with eGFR ≥90 mL/min/1.73 m^2. There are limited data available in patients with eGFR 30 to <60 mL/min/1.73 m^2 and no data available in patients with eGFR <30 mL/min/1.73 m^2.

Drug Interaction Studies

Clinical Studies and Model-Based Approaches

Effect of Strong CYP3A Inhibitors on AQVESME

Itraconazole (a strong CYP3A inhibitor) increased mitapivat AUCinf and Cmax by 4.9-fold and 1.7-fold, respectively, following a single AQVESME dose of 20 mg. Itraconazole increased mitapivat AUC0-12 and Cmax by 1.9‑fold and 1.6-fold, respectively, following AQVESME 100 mg twice daily. Ketoconazole (a strong CYP3A inhibitor) increased mitapivat AUC0-12 and Cmax by approximately 3.9-fold and 2.4-fold, respectively, following AQVESME 100 mg twice daily.

Effect of Moderate CYP3A Inhibitors on AQVESME

Fluconazole (a moderate CYP3A inhibitor) increased mitapivat AUC0-12 and Cmax by 2.7-fold and 1.7-fold, respectively, following AQVESME 100 mg twice daily.

Effect of Strong CYP3A Inducers on AQVESME

Rifampin (a strong CYP3A inducer) decreased mitapivat AUCinf and Cmax by 91% and 77%, respectively, following a single AQVESME dose of 50 mg. Rifampin decreased mitapivat AUC0-12 and Cmax by 93% and 82%, respectively, following AQVESME 100 mg twice daily.

Effect of Moderate CYP3A Inducers on AQVESME

Efavirenz (a moderate CYP3A4 inducer) decreased mitapivat AUC0-12 and Cmax by 52% and 21%, respectively, following AQVESME 100 mg twice daily.

Effect of AQVESME on CYP3A substrates

Midazolam (a CYP3A substrate) AUCinf and Cmax decreased by 65% and 59%, respectively, with AQVESME 100 mg twice daily.

Effect of AQVESME on P-gp Substrates

Co-administration of AQVESME with drugs that are substrates of P-gp may result in a clinically relevant increase in plasma concentrations of these substrates.

In vitro Studies

CYP450 and UGT Enzymes

Mitapivat induces CYP2B6, CYP2C8, CYP2C9, CYP2C19, and UGT1A1.

Drug Transporter Systems

Mitapivat is a substrate and an inhibitor of P-gp.

13 NONCLINICAL TOXICOLOGY

13.1 Carcinogenesis, Mutagenesis, Impairment of Fertility

Carcinogenesis

Mitapivat was not carcinogenic in transgenic rasH2 mice up to the highest doses tested at 500 mg/kg/day in males and at 250 mg/kg/day in females when given orally for 26 weeks.

Mitapivat was not carcinogenic in rats when given orally up to 300 mg/kg/day in males and 200 mg/kg/day in females, at systemic exposures 35 times and >86 times the MRHD, respectively, based on AUC.

Mutagenesis

Mitapivat was not mutagenic in an in vitro bacterial reverse mutation (Ames) assay. Mitapivat was not clastogenic in an in vitro human lymphocyte micronucleus assay or in an in vivo rat bone marrow micronucleus assay.

Fertility

In a fertility and early embryonic development study, oral administration of mitapivat twice daily in male rats prior to and during mating at doses up to 300 mg/kg/day, which represents 34 times the MRHD of 100 mg twice daily, based on AUC, did not result in adverse effects on fertility or reproductive function. In female rats, twice daily oral administration of mitapivat prior to mating and continuing through organogenesis, at doses up to 200 mg/kg/day, which represents 37 times the MRHD of 100 mg twice daily, based on AUC, did not result in adverse effects on fertility or reproductive function.

14 CLINICAL STUDIES

Patients with Transfusion-Dependent and Non-Transfusion-Dependent alpha- or beta-Thalassemia

Transfusion-Dependent alpha- or beta-Thalassemia

The efficacy of AQVESME was evaluated in ENERGIZE-T, a multinational, randomized, double-blind, placebo-controlled clinical study (NCT04770779) of 258 adult patients with transfusion-dependent alpha- or beta-thalassemia, defined as having had 6 to 20 RBC units transfused and no longer than a 6-week transfusion-free period during the 24 weeks prior to randomization. Patients were included if they had a documented diagnosis of thalassemia (beta-thalassemia with or without alpha-globin gene mutations, HbE/beta-thalassemia, or alpha-thalassemia/HbH disease). Randomization was stratified by geographical region (North America and Europe vs Asia-Pacific vs Rest of World) and thalassemia genotype (β^0/β^0 vs non-β^0/β^0).

Among the 258 patients with transfusion-dependent alpha- or beta-thalassemia, 171 patients were randomized to receive 100 mg of AQVESME twice daily during the 48-week double-blind period.

The median duration of treatment with AQVESME was 48.1 weeks (range: 0.3 to 59.9 weeks). Overall, 104 (60.5%) patients were exposed to AQVESME for >48 weeks. Among the 258 randomized patients, the median age was 33.5 years (range: 18 to 67) and 47.3% were male; 62.0% were from North America and Europe, 18.2% were from Asia-Pacific, and 19.8% were from the rest of the world; race was reported in 95.7% of patients: 60.1% White, 30.2% Asian, 0.8% Black or African American, 0.8% Multiracial, and 3.9% unknown.

The baseline disease characteristics are shown in Table 4.

Table 4: Baseline Disease Characteristics in Patients with Transfusion-Dependent Thalassemia (ENERGIZE-T)
Baseline Disease Characteristics | AQVESME N=171 | Placebo N=87 | Total N=258
Hemoglobin (g/dL), na Median (min, max) | 9.0 (5.1, 11.8) | 8.9 (5.1, 10.9) | 8.9 (5.1, 11.8)
Thalassemia Genotype, n (%) beta^0/ beta^0 non-beta^0/ beta^0 | 75 (44) 96 (56) | 39 (45) 48 (55) | 114 (44) 144 (56)
Transfusion Burden (RBC units), n (%)b ≤12 >12 | 54 (32) 117 (68) | 21 (24) 66 (76) | 75 (29) 183 (71)
Hepatic Iron Concentration (mg/g), n Median (min, max) | 133 4.58 (0.37, 28.21) | 74 4.43 (0.37, 20.47) | 207 4.55 (0.37, 28.21)
Prior History of Splenectomy, n (%) | 92 (54) | 49 (56) | 141 (55)
Prior History of Cholecystectomy, n (%) | 42 (25) | 24 (28) | 66 (26)
Prior History of Iron Chelation, n (%) | 165 (96) | 87 (100) | 252 (98)
Prior History of Hydroxyurea, n (%) | 7 (4.1) | 3 (3.4) | 10 (3.9)
Hb: hemoglobin, RBC: red blood cells
a Pretransfusion Hb threshold is the mean of all pretransfusion Hb concentrations for the RBC transfusions administered during the 24-week period before randomization.
b Total number of RBC units transfused in the 24-week period before randomization.

Efficacy was based upon transfusion reduction response, defined as ≥50% reduction in the number of red blood cell units transfused with a reduction of at least 2 units of RBCs transfused in any consecutive 12-week period through Week 48 compared with baseline. The efficacy results are shown in Table 5.

Table 5: Efficacy Results in Patients with Transfusion-Dependent Thalassemia (ENERGIZE T)
 | AQVESME N= 171 | Placebo N=87 | Difference
Endpoints | n (%) | n (%) | Adjusted Rate Differencea (%) (95% CI) | p-valueb
≥50% reduction from baseline in RBC units transfused in any consecutive 12 weeks, with a reduction of at least 2 units | 52 (30.4) | 11 (12.6) | 17.6 (8.0, 27.2) | 0.0003
Endpoints | n (%) | n (%) | Adjusted Rate Differenceb (%) (95% CI) | p-valuea
≥50% reduction from baseline in RBC units transfused in any consecutive 24 weeks | 23 (13.5) | 2 (2.3) | 11.1 (5.1, 17.0) | 0.0003
≥33% reduction from baseline in RBC units from Week 13 through Week 48 | 25 (14.6) | 1 (1.1) | 13.4 (7.7, 19.1) | <0.0001
≥50% reduction from baseline in RBC units from Week 13 through Week 48 | 13 (7.6) | 1 (1.1) | 6.4 (1.9, 10.9) | 0.0056
CI: confidence interval, RBC: red blood cell
a All p-values are 2-sided and all results are statistically significant.
b The difference is adjusted for randomization stratification factors, which included geographical region (North America and Europe vs Asia-Pacific vs Rest of World) and thalassemia genotype (β^0/β^0 vs non-β^0/β^0). The two-sided p-value is based on the Mantel-Haenszel stratum weighted method adjusting for the randomization stratification factors.

Non-Transfusion-Dependent alpha- or beta-Thalassemia

The efficacy of AQVESME was evaluated in ENERGIZE, a multinational, randomized, double-blind, placebo-controlled clinical study (NCT04770753) of 194 adults with non-transfusion-dependent alpha- or beta-thalassemia, defined as having had no more than 5 RBC units transfused during the 24‑week period prior to randomization and no RBC transfusions within 8 weeks prior to informed consent and during the screening period. Patients were included if they had a documented diagnosis of thalassemia (beta-thalassemia with or without alpha-globin gene mutations, HbE/beta-thalassemia, or alpha-thalassemia/HbH disease) and a baseline Hb concentration ≤10 g/dL. Randomization was stratified by baseline Hb concentrations (≤9 g/dL vs 9.1-10 g/dL) and thalassemia genotype (alpha-thalassemia/HbH disease vs beta-thalassemia).

Among the 194 patients with non-transfusion-dependent alpha- or beta-thalassemia, 130 patients were randomized to receive 100 mg of AQVESME twice daily during the 24-week double-blind period.

The median duration of treatment with AQVESME was 24.1 weeks (range: 1.1 to 28.1 weeks). Overall, 97 (75%) patients were exposed to AQVESME for >24 weeks. Among the 194 randomized patients, the median age was 41 years (range: 18 to 69) and 36.6% were male; race was reported in 99% of patients: 56.2% White, 39.2% Asian, 1.0% Black or African American, 0.5% Multiracial, and 2.1% unknown.

The baseline disease characteristics are shown in Table 6.

Table 6: Baseline Disease Characteristics in Patients with Non-Transfusion-Dependent Thalassemia (ENERGIZE)
Baseline Disease Characteristicsa | AQVESME N=130 | Placebo N=64 | Total N=194
Hemoglobin (g/dL), n Median (min, max) | 130 8.4 (5.3, 10.4) | 64 8.4 (5.9, 10.7) | 194 8.4 (5.3, 10.7)
Thalassemia Genotype, n (%) alpha-thalassemia/HbH disease beta-thalassemia | 42 (32) 88 (68) | 20 (31) 44 (69) | 62 (32) 132 (68)
Transfusion Burden (RBC units)b, n (%) 0 1-2 3-5 | 114 (87.7) 10 (7.7) 6 (4.6) | 54 (84.4) 7 (10.9) 3 (4.7) | 168 (86.6) 17 (8.8) 9 (4.6)
Reticulocyte (Fraction of 1), n Median (min, max) | 122 0.05 (0.00, 0.30) | 58 0.04 (0.00, 0.22) | 180 0.05 (0.00, 0.30)
Indirect Bilirubin (mg/dL), n Median (min, max) | 130 1.37 (0.13, 9.11) | 62 1.32 (0.15, 4.77) | 192 1.34 (0.13, 19.11)
LDH (U/L), n Median (min, max) | 130 264 (108, 1208) | 64 267 (110, 1009) | 194 265 (108, 1208)
Hepatic Iron Concentration (mg/g), n Median (min, max) | 98 3.93 (0.75, 27.19) | 52 2.76 (0.75, 18.53) | 150 3.64 (0.75, 27.19)
Prior History of Splenectomy, n (%) | 47 (36) | 25 (39) | 72 (37)
Prior History of Cholecystectomy, n (%) | 45 (35) | 16 (25) | 61 (31)
Prior History of Iron Chelation, n (%) | 46 (35) | 22 (34) | 68 (35)
Prior History of Hydroxyurea, n (%) | 11 (8.5) | 6 (9.4) | 17 (8.8)
Hb: hemoglobin, LDH: lactate dehydrogenase, RBC: red blood cell
a n is the number of patients with non-missing data.
b Total number of RBC units transfused in the 24-week period before randomization.

Efficacy was based upon Hb response, defined as a ≥1 g/dL increase in average Hb concentration from Week 12 through Week 24 compared with baseline and a mean change from baseline in fatigue-related symptoms and impacts assessed by a patient-reported outcome instrument, the Functional Assessment of Chronic Illness Therapy – Fatigue Scale (FACIT-Fatigue). See Table 7 for efficacy results.

Table 7: Efficacy Results in Patients with Non-Transfusion-Dependent Thalassemia (ENERGIZE)
 | AQVESME N= 130 | Placebo N=64 | Difference
Endpoint | n (%) | n (%) | Adjusted Rate Difference (%) (95% CI) | p-valuea
Hb Responseb | 55 (42.3) | 1 (1.6) | 40.9 (32.0, 49.8) | <0.0001
Endpoint | LS mean (95% CI) | LS mean (95% CI) | LS mean difference (95% CI) | p-valuea
Hemoglobin (g/dL)c | 0.86 (0.73, 0.99) | -0.11 (-0.28, 0.07) | 0.96 (0.78, 1.15) | <0.0001
FACIT-Fatigued | 4.85 (3.41, 6.30) | 1.46 (-0.43, 3.34) | 3.40 (1.21, 5.59) | 0.0026
CI: confidence interval, Hb: hemoglobin, LS: least squares
a All p-values are 2-sided and all results are statistically significant.
b For Hb response, the difference is adjusted for randomization stratification factors, which included Hb concentrations (≤9.0 g/dL vs 9.1-10.0 g/dL) and thalassemia genotype (alpha-thalassemia/HbH disease vs beta-thalassemia). The two‑sided p-value is based on the Mantel-Haenszel stratum weighted method adjusting for the randomization stratification factors.
c Change from baseline in average Hb concentration from Week 12 through Week 24.
d Change from baseline in average FACIT–Fatigue score from Week 12 through Week 24. FACIT-Fatigue total scores range from 0 to 52 with higher scores indicating less fatigue. At baseline, patients reported a mean FACIT-Fatigue score of approximately 36 in both the AQVESME and placebo arms.
Note: For the endpoints of change from baseline in average Hb concentration from Week 12 through Week 24 and change from baseline in average FACIT-Fatigue score from Week 12 through Week 24, the 95% CIs and the two-sided p-values are based on an analysis of covariance (ANCOVA) model, which included change from baseline as the dependent variable, treatment group as the independent variable, and baseline and the randomization stratification factors as covariates. The results are based on observed cases.

Eighty-seven percent of patients in the AQVESME arm experienced an increase from baseline in average Hb from Weeks 12 through 24 (see Figure 1). Figure 2 depicts change from baseline in hemoglobin over time.

Figure 1: Average Change from Baseline in Hemoglobin from Week 12 through Week 24 by Patient – All Randomized Patients (ENERGIZE)

Figure 2: Change from Baseline in Hemoglobin Over Time – All Randomized Patients (ENERGIZE)

Of the 55 patients with Hb response in the AQVESME arm, the average increase in Hb was 1.6 g/dL and the median duration of response was 19.6 weeks (range: 4.0 to 23.4+ weeks) during the 24-week double-blind period.

Patients in the AQVESME arm experienced an improvement compared to placebo in the change from baseline to Week 24 for 2 markers of hemolysis (indirect bilirubin [−0.62 mg/dL (95% CI: −0.80, −0.44)] and lactate dehydrogenase [−24.28 U/L (95% CI: −45.40, −3.15)]).

16 HOW SUPPLIED/STORAGE AND HANDLING

How Supplied

AQVESME 28-Day Packs
Tablet Strength | Package Configuration | Tablet Description | Tablet Imprint | NDC
100 mg | Carton containing 4 blister wallets. Each blister wallet contains 14 tablets. | Oblong, blue, film-coated tablets | "M100" printed on both sides | Carton: 71334-235-00 Blister wallet: 71334-235-14

Storage

Store in a refrigerator 2°C to 8°C (36°F to 46°F).

AQVESME may be stored at room temperature, 20°C to 25°C (68°F to 77°F) for up to 3 months. The discard date is 3 months after removal of the tablets from the refrigerator. Write the discard date in the space provided on the blister wallet and/or the carton. Discard the tablets if not used within 3 months or if the expiration date has passed, whichever occurs first. Dispense and store the blister wallets in the original carton until use.

17 PATIENT COUNSELING INFORMATION

Advise the patient to read the FDA-approved patient labeling (Medication Guide).

Hepatocellular Injury

Inform patients of the risk of hepatocellular injury with AQVESME. In patients with thalassemia treated with AQVESME, liver injury has been observed within the first 6 months of treatment. Tell patients to immediately report any new or worsening symptoms suggestive of liver injury including loss of appetite, nausea, right upper quadrant abdominal pain, vomiting, scleral icterus, jaundice, or dark urine on AQVESME treatment to their healthcare provider for further evaluation [see Warnings and Precautions (5.1)].

AQVESME REMS

AQVESME is only available through a restricted program called the AQVESME REMS [see Warnings and Precautions (5.2)].

Inform the patient of the following notable requirements:

- Patients must enroll in the REMS and comply with the REMS requirements.

AQVESME is available only from certified pharmacies participating in the REMS. Therefore, provide patients with the telephone number and website for information on how to obtain AQVESME.

Drug Interactions

Advise patients to inform their healthcare providers of all concomitant medications, including over-the-counter medications, vitamins, and herbal products [see Drug Interactions (7)].

Dosing and Storage Instructions

- Instruct patients to swallow the tablets whole with or without food and not to split, crush, chew, or dissolve the tablets.
- Advise patients if a dose of AQVESME is missed by 4 hours or less, to take the scheduled dose as soon as possible. If a dose of AQVESME is missed by more than 4 hours, advise the patient to not take a replacement dose and wait until the next scheduled dose.
- Advise patients to store AQVESME in a refrigerator at 2°C to 8°C (36°F to 46°F). Advise patients AQVESME may be stored at room temperature for up to 3 months. If removed from the refrigerator, advise the patient to store AQVESME at room temperature, 20°C to 25°C (68°F to 77°F), and record the discard date in the space provided in the blister wallet and/or the carton. The discard date is 3 months after removal of the tablets from the refrigerator. Advise the patient to discard the tablets by the written discard date or by the expiration date, whichever occurs first. Advise patients to store the blister wallets in the original carton until use.

AQVESMETM is a trademark of Agios Pharmaceuticals, Inc.

© 2025 Agios Pharmaceuticals, Inc.

Manufactured for and Distributed by:

Agios Pharmaceuticals, Inc.

Cambridge, MA 02139

AG-PI-003

MEDICATION GUIDE
AQVESME (ak ves’ mee)
(mitapivat)
tablets, for oral use

What is the most important information I should know about AQVESME?

AQVESME can cause serious side effects, including:

- Liver injury. AQVESME can cause serious liver injury. Liver injury has happened in people with thalassemia within the first 6 months of treatment with AQVESME. Your healthcare provider will do blood tests to check your liver before you start treatment with AQVESME, every 4 weeks for the first 24 weeks of treatment, and as needed. Your healthcare provider may temporarily or permanently stop your treatment with AQVESME if you have abnormal liver blood tests. Tell your healthcare provider right away if you develop any new or worsening signs or symptoms of liver problems including:

- loss of appetite
- nausea
- pain in the upper right side of your stomach area
- vomiting

- yellowing of the skin or white part of your eyes (jaundice)
- dark-colored urine

- Because of the risk of liver injury, AQVESME is only available through a restricted program called the AQVESME Risk Evaluation and Mitigation Strategy (REMS).

- Your healthcare provider must be enrolled in the AQVESME REMS for you to be prescribed AQVESME.
- Before you start treatment with AQVESME, you must enroll in the AQVESME REMS. Talk to your healthcare provider about how to enroll in the AQVESME REMS.
- Before you take AQVESME, your healthcare provider will make sure you understand how to take AQVESME safely, which will include liver tests when advised by your healthcare provider. Your healthcare provider will counsel you on the risk of liver injury and the REMS requirements.
- AQVESME can only be dispensed by a certified pharmacy that participates in the AQVESME REMS. Your healthcare provider can give you information on how to find a certified pharmacy.
- If you have any questions about the AQVESME REMS, ask your healthcare provider, go to www.aqvesmerems.com or call 1-800-625-9951.

See “What are the possible side effects of AQVESME?” for more information about side effects.

What is AQVESME?

AQVESME is a prescription medicine used to treat anemia (low red blood cells) in adults with alpha- or beta-thalassemia.

It is not known if AQVESME is safe and effective in children.

Before taking AQVESME, tell your healthcare provider about all of your medical conditions, including if you:

- have liver problems, such as cirrhosis.
- are pregnant or plan to become pregnant. It is not known if AQVESME will harm your unborn baby. Tell your healthcare provider right away if you become pregnant or think that you are pregnant during treatment with AQVESME.
- are breastfeeding or plan to breastfeed. It is not known if AQVESME passes into your breast milk. Talk to your healthcare provider about the best way to feed your baby during treatment with AQVESME.

Tell your healthcare provider about all the medicines that you take, including prescription and over-the- counter medicines, vitamins, and herbal supplements.

- Make sure to tell your healthcare provider if you take or use hormonal birth control (contraceptives). If you take or use hormonal birth control (except for intrauterine systems containing levonorgestrel), it may not work as well during treatment with AQVESME. Use a different type of birth control or use an additional nonhormonal birth control method (such as condoms) during treatment with AQVESME and for 28 days after stopping treatment with AQVESME.
- AQVESME and certain other medicines may affect each other and cause side effects.
- AQVESME may affect the way other medicines work, and other medicines may affect how AQVESME works.

Know the medicines you take. Keep a list of them to show your healthcare provider or pharmacist when you get a new medicine.

How should I take AQVESME?

- Take AQVESME exactly as your healthcare provider tells you to take it.
- Take AQVESME with or without food.
- Swallow AQVESME tablets whole. Do not split, crush, chew, or dissolve the tablets.
- If you miss a dose of AQVESME by 4 hours or less, take your dose as soon as possible. If more than 4 hours have passed since your regularly scheduled dose, do not take the missed dose and wait for the next dose. Return to your normal schedule at the next dose.

What are the possible side effects of AQVESME?

AQVESME can cause serious side effects:

- See “What is the most important information I should know about AQVESME?”

The most common side effects of AQVESME include headache and trouble sleeping (insomnia).

These are not all of the possible side effects of AQVESME.

Call your doctor for medical advice about side effects. You may report side effects to FDA at 1-800-FDA-1088.

How should I store AQVESME?

- Store AQVESME in a refrigerator between 36°F to 46°F (2°C to 8°C).
- You may also store AQVESME at room temperature between 68°F to 77°F (20°C to 25°C) for up to 3 months. If you remove AQVESME from the refrigerator, store AQVESME at room temperature.
  - Write the discard (throw away) date in the space provided on the blister wallet and the carton. The discard date is 3 months after you remove the tablets from the refrigerator.
  - Throw away AQVESME if not used by the written discard date or by the expiration date, whichever happens first.
- Store the blister wallets in the original carton until use.

Keep AQVESME and all medicines out of the reach of children.

General information about the safe and effective use of AQVESME.

Medicines are sometimes prescribed for purposes other than those listed in a Medication Guide. Do not use AQVESME for a condition for which it was not prescribed. Do not give AQVESME to other people, even if they have the same symptoms that you have. It may harm them. You can ask your pharmacist or healthcare provider for information about AQVESME that is written for health professionals.

What are the ingredients in AQVESME?

Active ingredients: mitapivat

Inactive ingredients: croscarmellose sodium, mannitol, microcrystalline cellulose, and sodium stearyl fumarate.

The tablet film-coating contains: FD&C Blue No. 2, hypromellose, lactose monohydrate, titanium dioxide, triacetin, and macrogol/PEG.

The tablet printed with blue ink contains: ammonium hydroxide, FD&C Blue No. 1, isopropyl alcohol, n-butyl alcohol, propylene glycol, shellac glaze, and titanium dioxide.

Manufactured for and Distributed by: Agios Pharmaceuticals, Inc., Cambridge, MA 02139

AQVESMETM is a trademark of Agios Pharmaceuticals, Inc.

© 2025 Agios Pharmaceuticals, Inc. All rights reserved.

For more information, visit www.aqvesme.com or call 1-833-228-8474.

This Medication Guide has been approved by the U.S. Food and Drug Administration. Issued: 12/2025

PRINCIPAL DISPLAY PANEL - 100 MG TABLET BLISTER PACK CARTON

NDC 71334-235-00

Do not use if seal
is broken or damaged

Rx Only

Aqvesme™
(mitapivat) tablets
100 mg per tablet

DISPENSE THE MEDICATION GUIDE
PROVIDED SEPARATELY TO EACH PATIENT

Swallow tablets whole. Do not split, crush, chew,
Or dissolve the tablets.

56 tablets

Contains 4-week supply of AQVESME™
(Four 7-day blister wallets with 14 tablets per wallet)